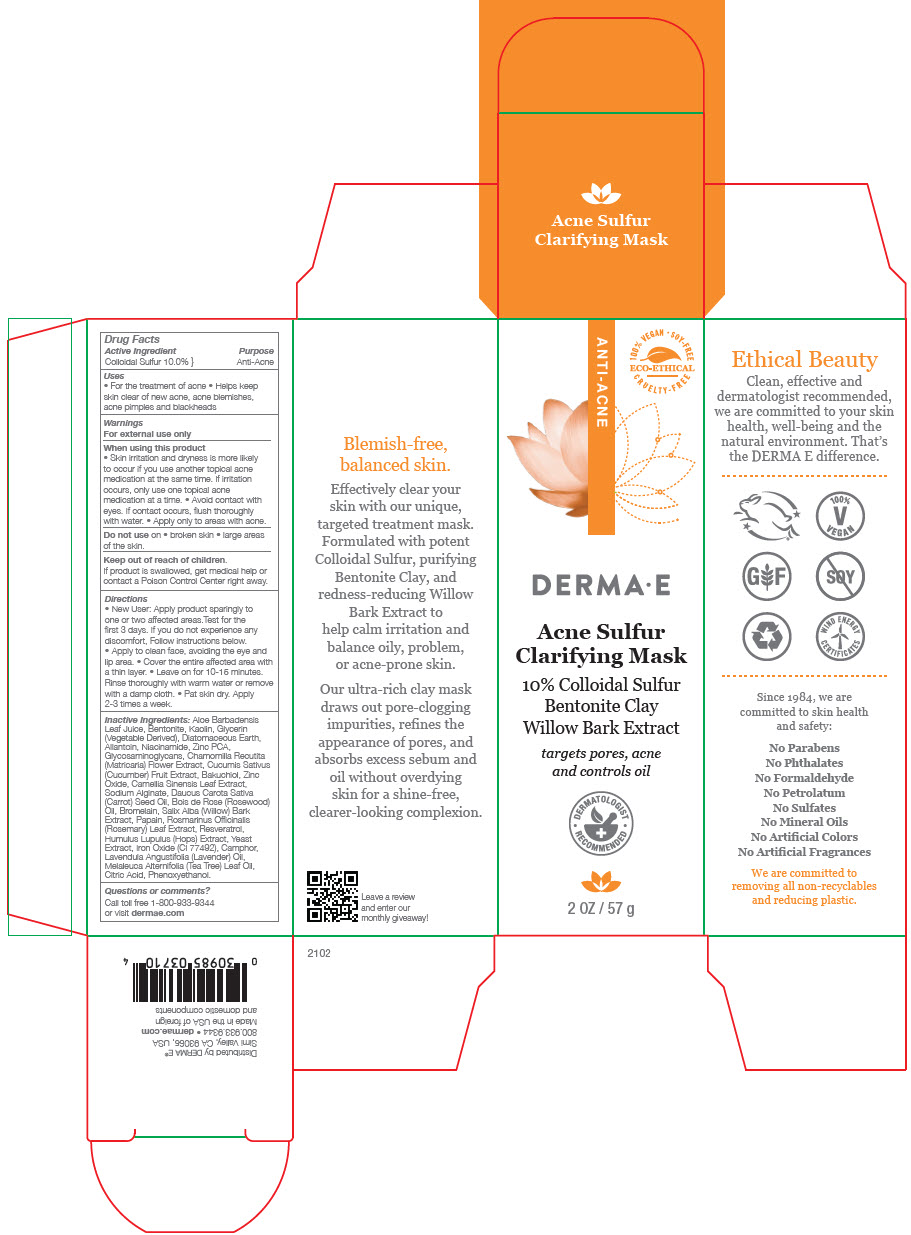 DRUG LABEL: Derma E Acne Clarifying Mask
NDC: 54108-3710 | Form: CREAM
Manufacturer: derma e
Category: otc | Type: HUMAN OTC DRUG LABEL
Date: 20230214

ACTIVE INGREDIENTS: SULFUR 100 mg/1 g
INACTIVE INGREDIENTS: ALOE VERA LEAF; KAOLIN; BENTONITE; GLYCERIN; DIATOMACEOUS EARTH; ALLANTOIN; NIACINAMIDE; ZINC PIDOLATE; CHAMOMILE; CUCUMBER; BAKUCHIOL; ZINC OXIDE; GREEN TEA LEAF; SODIUM ALGINATE; CARROT SEED OIL; ROSEWOOD OIL; BROMELAINS; SALIX ALBA BARK; PAPAIN; ROSEMARY; RESVERATROL; HOPS; YEAST, UNSPECIFIED; FERROUS OXIDE; SILICON DIOXIDE; CAMPHOR (SYNTHETIC); XANTHAN GUM; CETOSTEARYL ALCOHOL; CETEARYL GLUCOSIDE; LAVENDER OIL; TEA TREE OIL; CITRIC ACID MONOHYDRATE; PHENOXYETHANOL

Derma E Acne Clarifying Mask

Drug Facts

Active Ingredient

Colloidal Sulfur 10.0%

Purpose

Anti-Acne

Uses

- For the treatment of acne
- Helps keep skin clear of new acne, acne blemishes, acne pimples and blackheads

Warnings

For external use only

When using this product

- Skin irritation and dryness is more likely to occur if you use another topical acne medication at the same time. If irritation occurs, only use one topical acne medication at a time.
- Avoid contact with eyes. If contact occurs, flush thoroughly with water.
- Apply only to areas with acne.

Do not use on

- broken skin
- large areas of the skin.

Keep out of reach of children.

If product is swallowed, get medical help or contact a Poison Control Center right away.

Directions

- New User: Apply product sparingly to one or two affected areas.Test for the first 3 days. If you do not experience any discomfort, Follow instructions below.
- Apply to clean face, avoiding the eye and lip area.
- Cover the entire affected area with a thin layer.
- Leave on for 10-15 minutes. Rinse thoroughly with warm water or remove with a damp cloth.
- Pat skin dry. Apply 2-3 times a week.

Inactive Ingredients

Aloe Barbadensis Leaf Juice, Bentonite, Kaolin, Glycerin (Vegetable Derived), Diatomaceous Earth, Allantoin, Niacinamide, Zinc PCA, Glycosaminoglycans, Chamomilla Recutita (Matricaria) Flower Extract, Cucumis Sativus (Cucumber) Fruit Extract, Bakuchiol, Zinc Oxide, Camellia Sinensis Leaf Extract, Sodium Alginate, Daucus Carota Sativa (Carrot) Seed Oil, Bois de Rose (Rosewood) Oil, Bromelain, Salix Alba (Willow) Bark Extract, Papain, Rosmarinus Officinalis (Rosemary) Leaf Extract, Resveratrol, Humulus Lupulus (Hops) Extract, Yeast Extract, Iron Oxide (CI 77492), Camphor, Lavendula Angustifolia (Lavender) Oil, Melaleuca Alternifolia (Tea Tree) Leaf Oil, Citric Acid, Phenoxyethanol.

Questions or comments?

Call toll free 1-800-933-9344
or visit dermae.com

Distributed by DERMA E®
Simi Valley, CA 93065, USA

PRINCIPAL DISPLAY PANEL - 57 g Tube Box

ANTI-ACNE

100% VEGAN • SOY-FREE
CRUELTY-FREE

ECO-ETHICAL

DERMA • E

Acne Sulfur
Clarifying Mask

10% Colloidal Sulfur
Bentonite Clay
Willow Bark Extract

targets pores, acne
and controls oil

• DERMATOLOGIST
RECOMMENDED •

2 OZ / 57 g